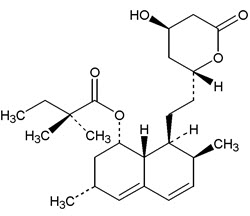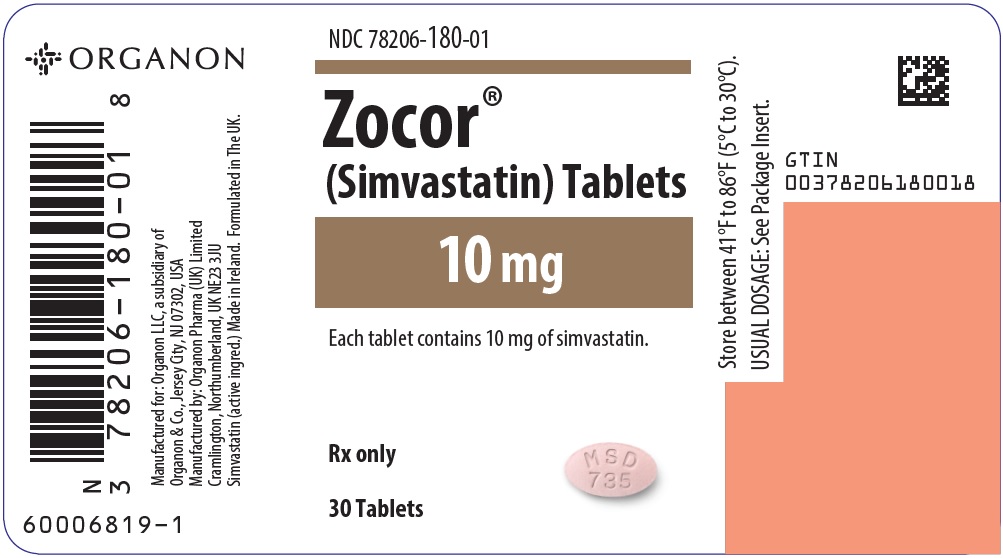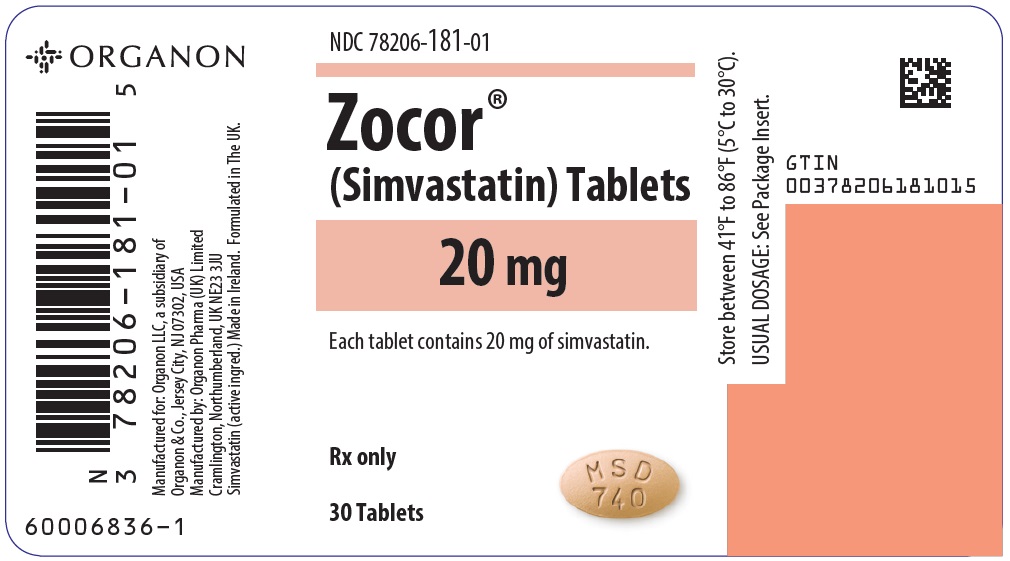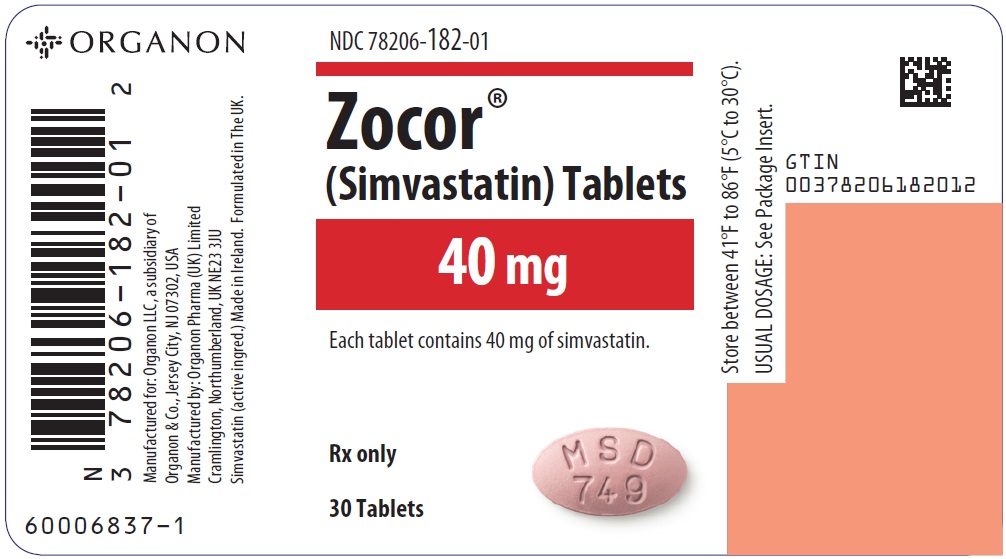 DRUG LABEL: ZOCOR
NDC: 78206-182 | Form: TABLET, FILM COATED
Manufacturer: Organon LLC
Category: prescription | Type: HUMAN PRESCRIPTION DRUG LABEL
Date: 20250328

ACTIVE INGREDIENTS: SIMVASTATIN 40 mg/1 1
INACTIVE INGREDIENTS: ASCORBIC ACID; BUTYLATED HYDROXYANISOLE; CITRIC ACID MONOHYDRATE; HYDROXYPROPYL CELLULOSE (1600000 WAMW); HYPROMELLOSE 2910 (6 MPA.S); FERRIC OXIDE RED; LACTOSE, UNSPECIFIED FORM; MAGNESIUM STEARATE; MICROCRYSTALLINE CELLULOSE; STARCH, CORN; TALC; TITANIUM DIOXIDE

HIGHLIGHTS OF PRESCRIBING INFORMATION

These highlights do not include all the information needed to use ZOCOR safely and effectively. See full prescribing information for ZOCOR.
ZOCOR® (simvastatin) tablets, for oral use
Initial U.S. Approval: 1991

RECENT MAJOR CHANGES

Dosage and Administration (2.1) | 3/2023

1 INDICATIONS AND USAGE

ZOCOR is an HMG-CoA reductase inhibitor indicated: (1)

- To reduce the risk of total mortality by reducing risk of coronary heart disease death, non-fatal myocardial infarction and stroke, and the need for coronary and non-coronary revascularization procedures in adults with established coronary heart disease, cerebrovascular disease, peripheral vascular disease, and/or diabetes, who are at high risk of coronary heart disease events.
- As an adjunct to diet to reduce low-density lipoprotein cholesterol (LDL-C):
  - In adults with primary hyperlipidemia.
  - In adults and pediatric patients aged 10 years and older with heterozygous familial hypercholesterolemia (HeFH).
- As an adjunct to other LDL-C-lowering therapies to reduce LDL-C in adults with homozygous familial hypercholesterolemia (HoFH).
- As an adjunct to diet for the treatment of adults with:
  - Primary dysbetalipoproteinemia.
  - Hypertriglyceridemia.

2 DOSAGE AND ADMINISTRATION

- Important Dosage and Administration Information: (2.1)
  - ZOCOR is no longer marketed in the 5 mg and 80 mg strengths. For dosing with the 5 mg strength, use another simvastatin product.
  - Take ZOCOR orally once daily in the evening.
  - Maximum recommended dosage is ZOCOR 40 mg once daily. An 80 mg daily dosage of ZOCOR is restricted to patients who have been taking simvastatin 80 mg daily chronically (e.g., for 12 months or more) without evidence of muscle toxicity.
  - For patients that require a high-intensity statin or are unable to achieve their LDL-C goal receiving ZOCOR 40 mg daily, prescribe alternative LDL-C lowering treatment.
  - Assess LDL-C when clinically appropriate, as early as 4 weeks after initiating, and adjust the dosage if necessary.
- Adults: Recommended dosage is 20 mg to 40 mg once daily. (2.2)
- Pediatric Patients Aged 10 Years and Older with HeFH: Recommended dosage is 10 mg to 40 mg once daily. (2.3)
- Patients with Severe Renal Impairment: Recommended starting dosage is simvastatin 5 mg once daily. (2.4, 8.6)
- See full prescribing information for ZOCOR dosage modifications due to drug interactions. (2.5)

3 DOSAGE FORMS AND STRENGTHS

Tablets: 10 mg; 20 mg; 40 mg (3)

The 5 mg and 80 mg strengths of ZOCOR are no longer marketed.

4 CONTRAINDICATIONS

- Concomitant use of strong CYP3A4 inhibitors (select azole anti-fungals, macrolide antibiotics, anti-viral medications, and nefazodone) (4, 7.1)
- Concomitant use of cyclosporine, danazol or gemfibrozil (4, 7.1)
- Acute liver failure or decompensated cirrhosis (4, 5.3)
- Hypersensitivity to simvastatin or any excipient in ZOCOR (4, 6.2)

5 WARNINGS AND PRECAUTIONS

- Myopathy and Rhabdomyolysis: Risk factors include age 65 years or greater, uncontrolled hypothyroidism, renal impairment, concomitant use with certain other drugs, and higher ZOCOR dosage. Chinese patients may be at higher risk for myopathy. Discontinue ZOCOR if markedly elevated CK levels occur or myopathy is diagnosed or suspected. Temporarily discontinue ZOCOR in patients experiencing an acute or serious condition at high risk of developing renal failure secondary to rhabdomyolysis. Inform patients of the risk of myopathy and rhabdomyolysis when starting or increasing ZOCOR dosage. Instruct patients to promptly report unexplained muscle pain, tenderness, or weakness, particularly if accompanied by malaise or fever. (5.1, 7.1, 8.5, 8.6, 8.8)
- Immune-Mediated Necrotizing Myopathy (IMNM): Rare reports of IMNM, an autoimmune myopathy, have been reported. Discontinue ZOCOR if IMNM is suspected. (5.2)
- Hepatic Dysfunction: Increases in serum transaminases have occurred, some persistent. Rare reports of fatal and non-fatal hepatic failure have occurred. Consider testing liver enzyme before initiating therapy and as clinically indicated thereafter. If serious hepatic injury with clinical symptoms and/or hyperbilirubinemia or jaundice occurs, promptly discontinue ZOCOR. (4, 5.3, 8.7)

6 ADVERSE REACTIONS

Most common adverse reactions (incidence ≥5%) are upper respiratory infection, headache, abdominal pain, constipation, and nausea. (6.1)

To report SUSPECTED ADVERSE REACTIONS, contact Organon LLC, a subsidiary of Organon & Co., at 1-844-674-3200 or FDA at 1-800-FDA-1088 or www.fda.gov/medwatch.

7 DRUG INTERACTIONS

- See full prescribing information for details regarding concomitant use of ZOCOR with other drugs or grapefruit juice that increase the risk of myopathy and rhabdomyolysis. (2.5, 7.1)
- Coumarin Anticoagulants: Obtain INR before ZOCOR initiation and monitor INR during ZOCOR dosage initiation or adjustment. (7.2)
- Digoxin: During ZOCOR initiation, monitor digoxin levels. (7.2)

8 USE IN SPECIFIC POPULATIONS

- Pregnancy: May cause fetal harm. (8.1)
- Lactation: Breastfeeding not recommended during treatment with ZOCOR. (8.2)

FULL PRESCRIBING INFORMATION

1 INDICATIONS AND USAGE

ZOCOR® is indicated:

- To reduce the risk of total mortality by reducing risk of coronary heart disease death, non-fatal myocardial infarction and stroke, and the need for coronary and non-coronary revascularization procedures in adults with established coronary heart disease, cerebrovascular disease, peripheral vascular disease, and/or diabetes, who are at high risk of coronary heart disease events.
- As an adjunct to diet to reduce low-density lipoprotein cholesterol (LDL-C):
  - In adults with primary hyperlipidemia.
  - In adults and pediatric patients aged 10 years and older with heterozygous familial hypercholesterolemia (HeFH).
- As an adjunct to other LDL-C-lowering therapies to reduce LDL-C in adults with homozygous familial hypercholesterolemia (HoFH).
- As an adjunct to diet for the treatment of adults with:
  - Primary dysbetalipoproteinemia.
  - Hypertriglyceridemia.

2 DOSAGE AND ADMINISTRATION

2.1 Important Dosage and Administration Information

- ZOCOR is no longer marketed in the 5 mg and 80 mg strengths. For dosing with the 5 mg strength, use another simvastatin product.
- Take ZOCOR orally once daily in the evening.
- The maximum recommended dosage is ZOCOR 40 mg once daily [see Dosage and Administration (2.2, 2.3)]. An 80 mg daily dosage of ZOCOR is restricted to patients who have been taking simvastatin 80 mg daily chronically (e.g., for 12 months or more) without evidence of muscle toxicity [see Warnings and Precautions (5.1)].
- If as dose is missed, take the missed dose as soon as possible. Do not double the next dose.
- For patients that require a high-intensity statin or are unable to achieve their LDL-C goal receiving ZOCOR 40 mg daily, prescribe alternative LDL-C-lowering treatment.
- Assess LDL-C when clinically appropriate, as early as 4 weeks after initiating ZOCOR, and adjust the dosage if necessary.

2.2 Recommended Dosage in Adult Patients

The recommended dosage range of ZOCOR is 20 mg to 40 mg once daily.

2.3 Recommended Dosage in Pediatric Patients 10 Years of Age and Older with HeFH

The recommended dosage range of ZOCOR is 10 mg to 40 mg daily.

2.4 Recommended Dosage in Patients with Renal Impairment

For patients with severe renal impairment [creatinine clearance (CLcr) 15 – 29 mL/min], the recommended starting dosage of simvastatin is 5 mg once daily [see Warnings and Precautions (5.1) and Use in Specific Populations (8.6)]. Use another simvastatin product to initiate dosing in such patients [see Dosage and Administration (2.1)].

There are no dosage adjustment recommendations for patients with mild or moderate renal impairment.

2.5 Dosage Modifications Due to Drug Interactions

Concomitant use of ZOCOR with the following drugs requires dosage modification of ZOCOR [see Warnings and Precautions (5.1) and Drug Interactions (7.1)].

Patients taking Lomitapide

Reduce the dosage of ZOCOR by 50%. Do not exceed ZOCOR 20 mg once daily (or 40 mg once daily for patients who have previously taken an 80 mg daily dosage of ZOCOR chronically while taking lomitapide) [see Dosage and Administration (2.1)].

Patients taking Verapamil, Diltiazem, or Dronedarone

Do not exceed ZOCOR 10 mg once daily.

Patients taking Amiodarone, Amlodipine, or Ranolazine

Do not exceed ZOCOR 20 mg once daily.

3 DOSAGE FORMS AND STRENGTHS

ZOCOR tablets:

- 10 mg: peach, oval tablets, marked MSD 735 on one side and plain on the other
- 20 mg: tan, oval tablets, marked MSD 740 on one side and plain on the other
- 40 mg: brick red, oval tablets, marked MSD 749 on one side and plain on the other

The 5 mg and 80 mg strengths of ZOCOR are no longer marketed.

4 CONTRAINDICATIONS

ZOCOR is contraindicated in the following conditions:

- Concomitant use of strong CYP3A4 inhibitors (select azole anti-fungals, macrolide antibiotics, anti-viral medications, and nefazodone) [see Drug Interactions (7.1)].
- Concomitant use of cyclosporine, danazol or gemfibrozil [see Drug Interactions (7.1)].
- Acute liver failure or decompensated cirrhosis [see Warnings and Precautions (5.3)].
- Hypersensitivity to simvastatin or any excipients in ZOCOR. Hypersensitivity reactions, including anaphylaxis, angioedema and Stevens-Johnson syndrome, have been reported [see Adverse Reactions (6.2)].

5 WARNINGS AND PRECAUTIONS

5.1 Myopathy and Rhabdomyolysis

ZOCOR may cause myopathy and rhabdomyolysis. Acute kidney injury secondary to myoglobinuria and rare fatalities have occurred as a result of rhabdomyolysis in patients treated with statins, including ZOCOR.

In clinical studies of 24,747 ZOCOR-treated patients with a median follow-up of 4 years, the incidence of myopathy, defined as unexplained muscle weakness, pain, or tenderness accompanied by creatinine kinase (CK) increases greater than ten times the upper limit of normal (10xULN), were approximately 0.03%, 0.08%, and 0.61% in patients treated with ZOCOR 20 mg, 40 mg, and 80 mg daily, respectively. In another clinical study of 12,064 ZOCOR-treated patients (with a history of myocardial infarction) with a mean follow-up of 6.7 years, the incidences of myopathy in patients taking ZOCOR 20 mg and 80 mg daily were approximately 0.02% and 0.9%, respectively. The incidences of rhabdomyolysis (defined as myopathy with a CK >40xULN) in patients taking ZOCOR 20 mg and 80 mg daily were approximately 0% and 0.4%, respectively [see Adverse Reactions (6.1)].

Risk Factors for Myopathy

Risk factors for myopathy include age 65 years or greater, uncontrolled hypothyroidism, renal impairment, concomitant use with certain other drugs (including other lipid-lowering therapies), and higher ZOCOR dosage; Chinese patients on ZOCOR may be at higher risk for myopathy [see Contraindications (4), Drug Interactions (7.1), and Use in Specific Populations (8.8)]. The risk of myopathy is increased by elevated plasma levels of simvastatin and simvastatin acid. The risk is also greater in patients taking an 80 mg daily dosage of ZOCOR compared with patients taking lower ZOCOR dosages and compared with patients using other statins with similar or greater LDL-C-lowering efficacy [see Adverse Reactions (6.1)].

Steps to Prevent or Reduce the Risk of Myopathy and Rhabdomyolysis

The concomitant use of strong CYP3A4 inhibitors with ZOCOR is contraindicated. If short-term treatment with strong CYP3A4 inhibitors is required, temporarily suspend ZOCOR during the duration of strong CYP3A4 inhibitor treatment. The concomitant use of ZOCOR with gemfibrozil, cyclosporine, or danazol is also contraindicated [see Contraindications (4) and Drug Interactions (7.1)].

ZOCOR dosage modifications are recommended for patients taking lomitapide, verapamil, diltiazem, dronedarone, amiodarone, amlodipine or ranolazine [see Dosage and Administration (2.5)]. ZOCOR use should be temporarily suspended in patients taking daptomycin. Lipid modifying doses (≥1 gram/day) of niacin, fibrates, colchicine, and grapefruit juice may also increase the risk of myopathy and rhabdomyolysis [see Drug Interactions (7.1)].

Use the 80 mg daily dosage of ZOCOR only in patients who have been taking simvastatin 80 mg daily chronically without evidence of muscle toxicity [see Dosage and Administration (2.1)]. If patients treated with an 80 mg daily dosage of ZOCOR are prescribed an interacting drug that increases the risk for myopathy and rhabdomyolysis, switch to an alternate statin [see Drug Interactions (7.1)].

Discontinue ZOCOR if markedly elevated CK levels occur or if myopathy is either diagnosed or suspected. Muscle symptoms and CK increases may resolve if ZOCOR is discontinued. Temporarily discontinue ZOCOR in patients experiencing an acute or serious condition at high risk of developing renal failure secondary to rhabdomyolysis, e.g., sepsis; shock; severe hypovolemia; major surgery; trauma; severe metabolic, endocrine, or electrolyte disorders; or uncontrolled epilepsy.

Inform patients of the risk of myopathy and rhabdomyolysis when starting or increasing the ZOCOR dosage and advise patients receiving an 80 mg daily dosage of ZOCOR of the increased risk of myopathy and rhabdomyolysis. Instruct patients to promptly report any unexplained muscle pain, tenderness or weakness, particularly if accompanied by malaise or fever.

5.2 Immune-Mediated Necrotizing Myopathy

There have been rare reports of immune-mediated necrotizing myopathy (IMNM), an autoimmune myopathy, associated with statin use, including reports of recurrence when the same or a different statin was administered. IMNM is characterized by proximal muscle weakness and elevated serum creatine kinase that persist despite discontinuation of statin treatment; positive anti-HMG CoA reductase antibody; muscle biopsy showing necrotizing myopathy without significant inflammation; and improvement with immunosuppressive agents. Additional neuromuscular and serologic testing may be necessary. Treatment with immunosuppressive agents may be required. Discontinue ZOCOR if IMNM is suspected.

5.3 Hepatic Dysfunction

Increases in serum transaminases have been reported with use of ZOCOR [see Adverse Reactions (6.1)]. In most cases, these changes appeared soon after initiation, were transient, were not accompanied by symptoms, and resolved or improved on continued therapy or after a brief interruption in therapy. Persistent increases to more than 3xULN in serum transaminases have occurred in approximately 1% of patients receiving ZOCOR in clinical studies. Marked persistent increases of hepatic transaminases have also occurred with ZOCOR. There have been rare postmarketing reports of fatal and non-fatal hepatic failure in patients taking statins, including ZOCOR.

Patients who consume substantial quantities of alcohol and/or have a history of liver disease may be at increased risk for hepatic injury.

Consider liver enzyme testing before ZOCOR initiation and when clinically indicated thereafter. ZOCOR is contraindicated in patients with acute liver failure or decompensated cirrhosis [see Contraindications (4)]. If serious hepatic injury with clinical symptoms and/or hyperbilirubinemia or jaundice occurs, promptly discontinue ZOCOR.

5.4 Increases in HbA1c and Fasting Serum Glucose Levels

Increases in HbA1c and fasting serum glucose levels have been reported with statins, including ZOCOR. Optimize lifestyle measures, including regular exercise, maintaining a healthy body weight, and making healthy food choices.

6 ADVERSE REACTIONS

The following important adverse reactions are described below and elsewhere in the labeling:

- Myopathy and Rhabdomyolysis [see Warnings and Precautions (5.1)]
- Immune-Mediated Necrotizing Myopathy [see Warnings and Precautions (5.2)]
- Hepatic Dysfunction [see Warnings and Precautions (5.3)]
- Increases in HbA1c and Fasting Serum Glucose Levels [see Warnings and Precautions (5.4)]

6.1 Clinical Trials Experience

Because clinical studies are conducted under widely varying conditions, adverse reaction rates observed in the clinical studies of a drug cannot be directly compared to rates in the clinical studies of another drug and may not reflect the rates observed in practice.

In clinical studies, 2,423 adult patients were exposed to ZOCOR with a median duration of follow-up of approximately 18 months. The most commonly reported adverse reactions (incidence ≥5%) in these ZOCOR clinical studies were: upper respiratory infections (9%), headache (7%), abdominal pain (7%), constipation (7%), and nausea (5%). Overall, 1.4% of patients discontinued ZOCOR due to adverse reactions. The most common adverse reactions that led to discontinuation were: gastrointestinal disorders (0.5%), myalgia (0.1%), and arthralgia (0.1%).

In a Cardiovascular Outcomes Study (the Scandinavian Simvastatin Survival Study [Study 4S]), adult patients (age range 35-71 years, 19% women, 100% Caucasians) were treated with 20-40 mg per day of ZOCOR or placebo over a median of 5.4 years [see Clinical Studies (14)]; adverse reactions reported in ≥2% of patients and at a rate greater than placebo are shown in Table 1.

Table 1: Adverse Reactions Reported ≥2% of Patients Treated with ZOCOR and Greater than Placebo in Study 4S
 | % Placebo (N = 2,223) | % ZOCOR (N = 2,221)
Bronchitis | 6.3 | 6.6
Abdominal pain | 5.8 | 5.9
Atrial fibrillation | 5.1 | 5.7
Gastritis | 3.9 | 4.9
Eczema | 3.0 | 4.5
Vertigo | 4.2 | 4.5
Diabetes mellitus | 3.6 | 4.2
Insomnia | 3.8 | 4.0
Myalgia | 3.2 | 3.7
Urinary tract infection | 3.1 | 3.2
Edema/swelling | 2.3 | 2.7
Headache | 2.1 | 2.5
Sinusitis | 1.8 | 2.3
Constipation | 1.6 | 2.2

Myopathy/Rhabdomyolysis

In clinical studies with a median follow-up of at least 4 years, in which 24,747 patients received ZOCOR , the incidence of myopathy (defined as unexplained muscle weakness, pain, or tenderness accompanied by CK increases greater than 10xULN) was approximately 0.03%, 0.08%, and 0.61% for the ZOCOR 20 mg, 40 mg, and 80 mg daily groups, respectively.

In a clinical outcomes study in which 12,064 adult patients with a history of myocardial infarction were treated with ZOCOR (mean follow-up 6.7 years), the incidence of myopathy (defined as unexplained muscle weakness or pain with a serum CK >10x [1200 U/L] ULN) in patients taking ZOCOR 20 mg and 80 mg daily was approximately 0.02% and 0.9%, respectively. The incidence of rhabdomyolysis (defined as myopathy with a CK >40xULN) in patients on ZOCOR 20 mg and 80 mg daily was approximately 0% and 0.4%, respectively. The incidence of myopathy and rhabdomyolysis were highest during the first year and then decreased during the subsequent years of treatment.

In another clinical outcomes study in which 10,269 adult patients were treated with ZOCOR 40 mg per day (mean follow-up of 5 years), the incidence of myopathy/rhabdomyolysis was <0.1% in patients treated with ZOCOR.

Elevations in Liver Enzyme Tests

Moderate (less than 3xULN) elevations of serum transaminases have been reported with use of ZOCOR.

Persistent increases to more than 3xULN in serum transaminases have occurred in approximately 1% of patients receiving ZOCOR in clinical studies. Marked persistent increases of hepatic transaminases have occurred with ZOCOR. Elevated alkaline phosphatase and γ-glutamyl transpeptidase have also been reported.

In Study 4S, with a median follow-up of 5.4 years, 1,986 adult patients were treated with ZOCOR 20 mg once daily, of whom 37% titrated to 40 mg once daily. The percentage of patients with one or more occurrences of transaminase elevations to >3xULN was 0.7% in patients taking ZOCOR compared with 0.6% in patients taking placebo. Elevated transaminases leading to discontinuation of study treatment occurred in 0.4% of patients taking ZOCOR and 0.2% of patients taking placebo. The majority of elevated transaminases leading to treatment discontinuation occurred within in the first year.

Adverse Reactions in Pediatric Patients with Heterozygous Familial Hypercholesterolemia

In a 48-week clinical study in pediatric patients 10 years of age and older (43% female, 97.7% Caucasians, 1.7% Hispanics, 0.6% Multiracial) with HeFH (n=175), treated with placebo or ZOCOR (10-40 mg daily), the most common adverse reactions were upper respiratory infection, headache, abdominal pain, and nausea [see Use in Specific Populations (8.4) and Clinical Studies (14)].

6.2 Postmarketing Experience

The following adverse reactions have been identified during post-approval use of ZOCOR. Because these reactions are reported voluntarily from a population of uncertain size, it is not always possible to reliably estimate their frequency or establish a causal relationship to drug exposure.

Body as whole: fever, chills, malaise, asthenia

Blood and Lymphatic System Disorders: anemia, thrombocytopenia, leukopenia, hemolytic anemia, positive ANA, ESR increase, eosinophilia

Gastrointestinal Disorders: pancreatitis, vomiting

Hepatic and Pancreatic Disorders: hepatitis/jaundice, fatal and non-fatal hepatic failure

Immune System Disorders: hypersensitivity syndrome including: anaphylaxis, angioedema, lupus erythematous-like syndrome, dermatomyositis, vasculitis

Musculoskeletal and Connective Tissue Disorders: muscle cramps, immune-mediated necrotizing myopathy, polymyalgia rheumatica, arthritis

Nervous System Disorders: dizziness, depression, paresthesia, peripheral neuropathy. Rare reports of cognitive impairment (e.g., memory loss, forgetfulness, amnesia, memory impairment, confusion) associated with statin use. Cognitive impairment was generally nonserious, and reversible upon statin discontinuation, with variable times to symptom onset (1 day to years) and symptom resolution (median of 3 weeks). There have been rare reports of new-onset or exacerbation of myasthenia gravis, including ocular myasthenia, and reports of recurrence when the same or a different statin was administered.

Skin and Subcutaneous Tissue Disorders: pruritus, alopecia, a variety of skin changes (e.g., nodules, discoloration, dryness of skin/mucous membranes, changes to hair/nails), purpura, lichen planus, urticaria, photosensitivity, flushing, toxic epidermal necrolysis, erythema multiforme, including Stevens-Johnson syndrome

Respiratory and Thoracic: interstitial lung disease, dyspnea

Reproductive System Disorders: erectile dysfunction

7 DRUG INTERACTIONS

7.1 Drug Interactions that Increase the Risk of Myopathy and Rhabdomyolysis with ZOCOR

ZOCOR is a substrate of CYP3A4 and of the transport protein OATP1B1. ZOCOR exposure can be significantly increased with concomitant administration of inhibitors of CYP3A4 and OATP1B1. Table 2 includes a list of drugs that increase the risk of myopathy and rhabdomyolysis when used concomitantly with ZOCOR and instructions for preventing or managing them [see Warnings and Precautions (5.1) and Clinical Pharmacology (12.3)].

Table 2: Drug Interactions that Increase the Risk of Myopathy and Rhabdomyolysis with ZOCOR
Strong CYP3A4 inhibitors
Clinical Impact: | Simvastatin is a substrate of CYP3A4. Concomitant use of strong CYP3A4 inhibitors with ZOCOR increases simvastatin exposure and increases the risk of myopathy and rhabdomyolysis, particularly with higher ZOCOR dosages.
Intervention: | Concomitant use of strong CYP3A4 inhibitors with ZOCOR is contraindicated [see Contraindications (4)]. If treatment with a CYP3A4 inhibitor is unavoidable, suspend ZOCOR during the course of strong CYP3A4 inhibitor treatment.
Examples: | Select azole anti-fungals (e.g., itraconazole, ketoconazole, posaconazole, and voriconazole), select macrolide antibiotics (e.g., erythromycin and clarithromycin), select HIV protease inhibitors (e.g., nelfinavir, ritonavir, and darunavir/ritonavir), select HCV protease inhibitors (e.g., boceprevir and telaprevir), cobicistat-containing products, and nefazodone.
Cyclosporine, Danazol, or Gemfibrozil
Clinical Impact: | The risk of myopathy and rhabdomyolysis is increased with concomitant use of cyclosporine, danazol, or gemfibrozil with ZOCOR. Gemfibrozil may cause myopathy when given alone.
Intervention: | Concomitant use of cyclosporine, danazol, or gemfibrozil with ZOCOR is contraindicated [see Contraindications (4)].
Amiodarone, Dronedarone, Ranolazine, or Calcium Channel Blockers
Clinical Impact: | The risk of myopathy and rhabdomyolysis is increased by concomitant use of amiodarone, dronedarone, ranolazine, or calcium channel blockers with ZOCOR.
Intervention: | For patients taking verapamil, diltiazem, or dronedarone, do not exceed ZOCOR 10 mg daily. For patients taking amiodarone, amlodipine, or ranolazine, do not exceed ZOCOR 20 mg daily [see Dosage and Administration (2.5)].
Lomitapide
Clinical Impact: | Simvastatin exposure is approximately doubled with concomitant use of lomitapide and the risk of myopathy and rhabdomyolysis is increased.
Intervention: | Reduce the dose of ZOCOR by 50% if initiating lomitapide. Do not exceed ZOCOR 20 mg daily (or ZOCOR 40 mg daily for patients who have previously taken an 80 mg daily dosage of ZOCOR chronically) while taking lomitapide [see Dosage and Administration (2.1, 2.5)].
Daptomycin
Clinical Impact: | Cases of rhabdomyolysis have been reported with simvastatin administered with daptomycin. Both ZOCOR and daptomycin can cause myopathy and rhabdomyolysis when given alone and the risk of myopathy and rhabdomyolysis may be increased by coadministration.
Intervention: | If treatment with daptomycin is required, consider temporarily suspending ZOCOR during the course of daptomycin treatment.
Niacin
Clinical Impact: | Cases of myopathy and rhabdomyolysis have been observed with concomitant use of lipid modifying dosages of niacin-containing products (≥1 gram/day niacin) with ZOCOR. The risk of myopathy is greater in Chinese patients. In a clinical study (median follow-up 3.9 years) of patients at high risk of CVD and with well-controlled LDL-C levels on simvastatin 40 mg/day with or without ezetimibe 10 mg/day, there was no incremental benefit on cardiovascular outcomes with the addition of lipid-modifying doses of niacin.
Intervention: | Concomitant use of ZOCOR with lipid-modifying dosages of niacin is not recommended in Chinese patients [see Use in Specific Populations (8.8)]. For non-Chinese patients, consider if the benefit of using lipid-modifying doses of niacin concomitantly with ZOCOR outweighs the increased risk of myopathy and rhabdomyolysis. If concomitant use is decided, monitor patients for signs and symptoms of myopathy, particularly during initiation of therapy and during upward dose titration of either drug.
Fibrates (other than Gemfibrozil)
Clinical Impact: | Fibrates may cause myopathy when given alone. The risk of myopathy and rhabdomyolysis is increased with concomitant use of fibrates with ZOCOR.
Intervention: | Consider if the benefit of using fibrates concomitantly with ZOCOR outweighs the increased risk of myopathy and rhabdomyolysis. If concomitant use is decided, monitor patients for signs and symptoms of myopathy, particularly during initiation of therapy and during upward dose titration of either drug.
Colchicine
Clinical Impact: | Cases of myopathy and rhabdomyolysis have been reported with concomitant use of colchicine with ZOCOR.
Intervention: | Consider if the benefit of using colchicine concomitantly with ZOCOR outweighs the increased risk of myopathy and rhabdomyolysis. If concomitant use is decided, monitor patients for signs and symptoms of myopathy, particularly during initiation of therapy and during upward dose titration of either drug.
Grapefruit Juice
Clinical Impact: | Grapefruit juice can raise the plasma levels of simvastatin and may increase the risk of myopathy and rhabdomyolysis.
Intervention: | Avoid grapefruit juice when taking ZOCOR.

7.2 ZOCOR Effects on Other Drugs

Table 3 presents ZOCOR’s effect on other drugs and instructions for preventing or managing them.

Table 3: ZOCOR Effects on Other Drugs
Coumarin Anticoagulants
Clinical Impact: | ZOCOR may potentiate the effect of coumarin anticoagulants and increase the INR. The concomitant use of ZOCOR (20 to 40 mg) and coumarin anticoagulants increased the INR from a baseline of 1.7 to 1.8 in healthy subjects and from 2.6 to 3.4 in patients with hyperlipidemia. There are postmarketing reports of clinically evident bleeding and/or increased INR in patients taking concomitant statins and warfarin.
Intervention: | In patients taking coumarin anticoagulants, obtain an INR before starting ZOCOR and frequently enough after initiation, dose titration, or discontinuation to ensure that no significant alteration in INR occurs. Once the INR is stable, monitor INR at regularly recommended intervals.
Digoxin
Clinical Impact: | Concomitant use of digoxin with ZOCOR may result in elevated plasma digoxin concentrations [see Clinical Pharmacology (12.3)].
Intervention: | Monitor digoxin levels in patients taking digoxin when ZOCOR is initiated.

8 USE IN SPECIFIC POPULATIONS

8.1 Pregnancy

Risk Summary

Discontinue ZOCOR when pregnancy is recognized. Alternatively, consider the ongoing therapeutic needs of the individual patient.

ZOCOR decreases synthesis of cholesterol and possibly other biologically active substances derived from cholesterol; therefore, ZOCOR may cause fetal harm when administered to pregnant patients based on the mechanism of action [see Clinical Pharmacology (12.1)]. In addition, treatment of hyperlipidemia is not generally necessary during pregnancy. Atherosclerosis is a chronic process and the discontinuation of lipid-lowering drugs during pregnancy should have little impact on the outcome of long-term therapy of primary hyperlipidemia for most patients.

Available data from case series and prospective and retrospective observational cohort studies over decades of use with statins in pregnant women have not identified a drug-associated risk of major congenital malformations. Published data from prospective and retrospective observational cohort studies with ZOCOR use in pregnant women are insufficient to determine if there is a drug-associated risk of miscarriage (see Data).

In animal reproduction studies, no adverse developmental effects were observed in pregnant rats or rabbits orally administered simvastatin during the period of organogenesis at doses that resulted in 2.5 and 2 times, respectively, the human exposure at the maximum recommended human dosage of 80 mg/day, based on body surface area (mg/m^2) (see Data).

The estimated background risk of major birth defects and miscarriage for the indicated population is unknown. In the U.S. general population, the estimated background risk of major birth defects and miscarriage in clinically recognized pregnancies is 2 to 4% and 15 to 20%, respectively.

Data

Human Data

A Medicaid cohort linkage study of 1152 statin-exposed pregnant women compared to 886,996 controls did not find a significant teratogenic effect from maternal use of statins in the first trimester of pregnancy, after adjusting for potential confounders – including maternal age, diabetes mellitus, hypertension, obesity, and alcohol and tobacco use – using propensity score-based methods. The relative risk of congenital malformations between the group with statin use and the group with no statin use in the first trimester was 1.07 (95% confidence interval 0.85 to 1.37) after controlling for confounders, particularly pre-existing diabetes mellitus. There were also no statistically significant increases in any of the organ-specific malformations assessed after accounting for confounders. In the majority of pregnancies, statin treatment was initiated prior to pregnancy and was discontinued at some point in the first trimester when pregnancy was identified. Study limitations include reliance on physician coding to define the presence of a malformation, lack of control for certain confounders such as body mass index, use of prescription dispensing as verification for the use of a statin, and lack of information on non-live births.

Animal Data

Simvastatin was given to pregnant rats at doses of 6.25, 12.5 and 25 mg/kg/day (0.6 times, 1.3 times, and 2.5 times, respectively, the maximum recommended dosage of 80 mg/day when normalized to body surface area) from gestation days 6-17 and to pregnant rabbits from gestation days 6-18 at doses of 2.5, 5, and 10 mg/kg/day (0.5 times, 1 times, and 2 times, respectively, the maximum recommended dosage of 80 mg/day when normalized to body surface area). For both species, there was no evidence of maternal toxicity or embryolethality. In rats, mean fetal body weights in the 25 mg/kg/day group were decreased 5.4%. Similar fetal body weight effects were not observed in rabbits.

Simvastatin doses of 6.25, 12.5 and 25 mg/kg/day (0.6 times, 1.3 times, and 2.5 times, respectively, the maximum recommended dosage of 80 mg/day when normalized to body surface area) were given to pregnant rats from gestation day 15 to lactation day 21. Slight decreases in maternal body weight gain and pup postnatal day 0 weight were observed in the 25 mg/kg/day dose group. Mean body weight gain of pups during lactation was slightly decreased at doses ≥12.5 mg/kg/day. Post weaning weight, behavior, reproductive performance and fertility of the offspring were not affected at any dose tested.

Placental transfer of simvastatin was not evaluated in rats or rabbits. However, it has been shown that other drugs in this class cross the placenta.

8.2 Lactation

Risk Summary

There is no information about the presence of simvastatin in human or animal milk, the effects of the drug on the breastfed infant or the effects of the drug on milk production. However, it has been shown that another drug in this class passes into human milk. Statins, including ZOCOR, decrease cholesterol synthesis and possibly the synthesis of other biologically active substances derived from cholesterol and may cause harm to the breastfed infant.

Because of the potential for serious adverse reactions in a breastfed infant, based on the mechanism of action, advise patients that breastfeeding is not recommended during treatment with ZOCOR [see Use in Specific Populations (8.1), Clinical Pharmacology (12.1)].

8.4 Pediatric Use

The safety and effectiveness of ZOCOR as an adjunct to diet to reduce LDL-C have been established in pediatric patients 10 years of age and older with HeFH. Use of ZOCOR for this indication is based on a double-blind, placebo-controlled clinical study in 175 pediatric patients (99 boys and 76 girls at least 1 year post-menarche) 10 years of age and older with HeFH. In this limited controlled study, there was no significant effect on growth or sexual maturation in the boys or girls, or on menstrual cycle length in girls.

The safety and effectiveness of ZOCOR have not been established in pediatric patients younger than 10 years of age with HeFH or in pediatric patients with other types of hyperlipidemia (other than HeFH).

8.5 Geriatric Use

Of the total number of ZOCOR-treated patients in clinical studies 1,021 (23%) patients, 5,366 (52%) patients, and 363 (15%) patients were ≥65 years old, respectively. In Study HPS, 615 (6%) patients were ≥75 years old [see Clinical Studies (14)]. In a clinical study of patients treated with ZOCOR 80 mg daily, patients ≥65 years of age had an increased risk of myopathy, including rhabdomyolysis, compared to patients <65 years of age.

A pharmacokinetic study with ZOCOR use showed the mean plasma level of total inhibitors to be approximately 45% higher in geriatric patients between 70-78 years of age compared with patients between 18-30 years of age [see Clinical Pharmacology (12.3)].

Advanced age (≥65 years) is a risk factor for ZOCOR-associated myopathy and rhabdomyolysis. Dose selection for an elderly patient should be cautious, recognizing the greater frequency of decreased hepatic, renal, or cardiac function, and of concomitant disease or other drug therapy and the higher risk of myopathy. Monitor geriatric patients receiving ZOCOR for the increased risk of myopathy [see Warnings and Precautions (5.1)].

8.6 Renal Impairment

Renal impairment is a risk factor for myopathy and rhabdomyolysis. Monitor all patients with renal impairment for development of myopathy. In patients with severe renal impairment (CLcr 15 – 29 mL/min), the recommended starting dosage is simvastatin 5 mg once daily [see Dosage and Administration (2.4), Warnings and Precautions (5.1)]. The 5 mg strength of ZOCOR is no longer marketed. Use another simvastatin product to initiate dosing in such patients.

8.7 Hepatic Impairment

ZOCOR is contraindicated in patients with acute liver failure or decompensated cirrhosis [see Contraindications (4), Warnings and Precautions (5.3)].

8.8 Chinese Patients

In a clinical study in which patients at high risk of CVD were treated with simvastatin 40 mg/day (median follow-up 3.9 years), the incidence of myopathy was approximately 0.05% for non-Chinese patients (n=7367) compared with 0.24% for Chinese patients (n=5468). In this study, the incidence of myopathy for Chinese patients on simvastatin 40 mg/day or ezetimibe/simvastatin 10/40 mg/day coadministered with extended-release niacin 2 g/day was 1.24%.

Chinese patients may be at higher risk for myopathy, monitor these patients appropriately. Coadministration of ZOCOR with lipid-modifying doses of niacin-containing products (≥1 g/day niacin) is not recommended in Chinese patients [see Warnings and Precautions (5.1), Drug Interactions (7.1)].

10 OVERDOSAGE

No specific antidotes for ZOCOR are known. Contact Poison Control (1-800-222-1222) for latest recommendations.

11 DESCRIPTION

ZOCOR (simvastatin) is a prodrug of 3-hydoroxy-3-methylglutaryl coenzyme A (HMG-CoA) reductase inhibitor that is derived synthetically from a fermentation product of Aspergillus terreus.

Simvastatin is butanoic acid, 2,2-dimethyl-,1,2,3,7,8,8a-hexahydro-3,7-dimethyl-8-[2-(tetrahydro-4-hydroxy-6-oxo-2H-pyran-2-yl)-ethyl]-1-naphthalenyl ester, [1S-[1α,3α,7β,8β(2S*,4S*),-8aβ]]. The empirical formula of simvastatin is C25H38O5 and its molecular weight is 418.57. Its structural formula is:

Simvastatin is a white to off-white, nonhygroscopic, crystalline powder that is practically insoluble in water, and freely soluble in chloroform, methanol and ethanol.

ZOCOR tablets (simvastatin) are available for oral administration in strength of 10 mg, 20 mg, or 40 mg. Each tablet contains following inactive ingredients: ascorbic acid, citric acid, hydroxypropyl cellulose, hypromellose, iron oxides, lactose, magnesium stearate, microcrystalline cellulose, starch, talc, and titanium dioxide. Butylated hydroxyanisole is added as a preservative. The 5 mg and 80 mg strengths of ZOCOR are no longer marketed.

12 CLINICAL PHARMACOLOGY

12.1 Mechanism of Action

Simvastatin is a prodrug and is hydrolyzed to its active β-hydroxyacid form, simvastatin acid, after administration. Simvastatin acid and its metabolites are inhibitors of HMG-CoA reductase, the rate-limiting enzyme that converts HMG-CoA to mevalonate, a precursor of cholesterol.

12.2 Pharmacodynamics

Inhibition of HMG-CoA reductase by simvastatin acid accelerates the expression of LDL-receptors, followed by the uptake of LDL-C from blood to the liver, leading to a decrease in plasma LDL-C and total cholesterol. Sustained inhibition of cholesterol synthesis in the liver also decreases levels of very-low-density lipoproteins. The maximum LDL-C reduction of ZOCOR is usually achieved by 4 weeks and is maintained after that.

12.3 Pharmacokinetics

Simvastatin is a lactone that is readily hydrolyzed in vivo to the corresponding β-hydroxyacid. Pharmacokinetics (PK) of simvastatin and its metabolites was originally characterized using inhibition of HMG-CoA reductase activity following base hydrolysis of plasma samples, as specific bioanalytical methods were not available. Inhibition of the enzyme activity (equivalent to the level of total inhibitors) represented the combination of activities in plasma following administration of simvastatin from both active (simvastatin acid and its metabolites) and latent forms (simvastatin and its metabolites) after conversion to the active forms in the presence of base.

Absorption

Following an oral dose of ^14C-labeled simvastatin, plasma concentrations of total radioactivity (simvastatin plus ^14C-metabolites) peaked at 4 hours and declined rapidly to about 10% of peak by 12 hours postdose. Since simvastatin undergoes extensive first-pass extraction in the liver, the availability of simvastatin to the general circulation is low (<5%). PK, assessed as area under the concentrations of total inhibitors – time curve, was apparently linear with doses up to 120 mg.

Effect of Food

The plasma profile of total inhibitors concentration was not affected when simvastatin was administered with low fat meal.

Distribution

Both simvastatin and its β-hydroxyacid metabolite are highly bound (approximately 95%) to human plasma proteins.

Elimination

Metabolism

Simvastatin is metabolized by CYP3A4. The major active metabolites of simvastatin present in human plasma are simvastatin acid and its 6′-hydroxy, 6′-hydroxymethyl, and 6′-exomethylene derivatives. Peak plasma concentrations of both active and total inhibitors were attained within 1.3 to 2.4 hours postdose.

Excretion

Following an oral dose of ^14C-labeled simvastatin, 13% of the dose was excreted in urine and 60% in feces.

Specific Populations

Geriatric Patients

In a study including 16 geriatric patients between 70 and 78 years of age who received ZOCOR 40 mg/day, the mean plasma level of total inhibitors was increased approximately 45% compared with 18 patients between 18-30 years of age [see Use in Specific Populations (8.5)].

Drug Interaction Studies

Simvastatin acid is a substrate of the transport protein OATP1B1. Concomitant administration of inhibitors of the transport protein OATP1B1 and/or CYP3A4 may lead to increased exposure of simvastatin acid. Cyclosporine has been shown to increase the AUC of statins; although the mechanism is not fully understood, the increase in AUC for simvastatin acid is presumably due, in part, to inhibition of CYP3A4 and/or OATP1B1 [see Drug Interactions (7)].

Table 4 displays the effect of coadministered drugs or grapefruit juice on simvastatin systemic exposure [see Drug Interactions (7)].

Table 4: Effect of Coadministered Drugs or Grapefruit Juice on Simvastatin Systemic Exposure
Coadministered Drug or Grapefruit Juice | Dosing of Coadministered Drug or Grapefruit Juice | Dosing of Simvastatin | Geometric Mean Ratio (Ratio [Results based on a chemical assay except results with propranolol as indicated.] with / without coadministered drug) No Effect = 1.00
Coadministered Drug or Grapefruit Juice | Dosing of Coadministered Drug or Grapefruit Juice | Dosing of Simvastatin |  | AUC | Cmax
Telithromycin [Results could be representative of the following CYP3A4 inhibitors: ketoconazole, erythromycin, clarithromycin, HIV protease inhibitors, and nefazodone.] | 200 mg QD for 4 days | 80 mg | simvastatin acid [Simvastatin acid refers to the β-hydroxyacid of simvastatin.] simvastatin | 12 8.9 | 15 5.3
Nelfinavir | 1250 mg BID for 14 days | 20 mg QD for 28 days | simvastatin acid simvastatin | 6 | 6.2
Itraconazole | 200 mg QD for 4 days | 80 mg | simvastatin acid simvastatin |  | 13.1 13.1
Posaconazole | 100 mg (oral suspension) QD for 13 days | 40 mg | simvastatin acid simvastatin | 7.3 10.3 | 9.2 9.4
 | 200 mg (oral suspension) QD for 13 days | 40 mg | simvastatin acid simvastatin | 8.5 10.6 | 9.5 11.4
Gemfibrozil | 600 mg BID for 3 days | 40 mg | simvastatin acid simvastatin | 2.85 1.35 | 2.18 0.91
Grapefruit Juice [The effect of amounts of grapefruit juice between those used in these two studies on simvastatin pharmacokinetics has not been studied.] (high dose) | 200 mL of double-strength TID [Double-strength: one can of frozen concentrate diluted with one can of water. Grapefruit juice was administered TID for 2 days, and 200 mL together with single dose simvastatin and 30 and 90 minutes following single dose simvastatin on Day 3.] | 60 mg single dose | simvastatin acid simvastatin | 7 16
Grapefruit Juice (low dose) | 8 oz (about 237 mL) of single-strength [Single-strength: one can of frozen concentrate diluted with 3 cans of water. Grapefruit juice was administered with breakfast for 3 days, and simvastatin was administered in the evening on Day 3.] | 20 mg single dose | simvastatin acid simvastatin | 1.3 1.9
Verapamil SR | 240 mg QD Days 1-7 then 240 mg BID on Days 8-10 | 80 mg on Day 10 | simvastatin acid simvastatin | 2.3 2.5 | 2.4 2.1
Diltiazem | 120 mg BID for 10 days | 80 mg on Day 10 | simvastatin acid simvastatin | 2.69 3.10 | 2.69 2.88
Diltiazem | 120 mg BID for 14 days | 20 mg on Day 14 | simvastatin | 4.6 | 3.6
Dronedarone | 400 mg BID for 14 days | 40 mg QD for 14 days | simvastatin acid simvastatin | 1.96 3.90 | 2.14 3.75
Amiodarone | 400 mg QD for 3 days | 40 mg on Day 3 | simvastatin acid simvastatin | 1.75 1.76 | 1.72 1.79
Amlodipine | 10 mg QD × 10 days | 80 mg on Day 10 | simvastatin acid simvastatin | 1.58 1.77 | 1.56 1.47
Ranolazine SR | 1000 mg BID for 7 days | 80 mg on Day 1 and Days 6-9 | simvastatin acid simvastatin | 2.26 1.86 | 2.28 1.75
Lomitapide | 60 mg QD for 7 days | 40 mg single dose | simvastatin acid simvastatin | 1.7 2 | 1.6 2
Lomitapide | 10 mg QD for 7 days | 20 mg single dose | simvastatin acid simvastatin | 1.4 1.6 | 1.4 1.7
Fenofibrate | 160 mg QD × 14 days | 80 mg QD on Days 8-14 | simvastatin acid simvastatin | 0.64 0.89 | 0.89 0.83
Niacin extended-release | 2 g single dose | 20 mg single dose | simvastatin acid simvastatin | 1.6 1.4 | 1.84 1.08
Propranolol | 80 mg single dose | 80 mg single dose | total inhibitor | 0.79 | ↓ from 33.6 to 21.1 ng∙eq/mL
 |  |  | active inhibitor | 0.79 | ↓ from 7.0 to 4.7 ng∙eq/mL

ZOCOR’s Effect on the Pharmacokinetics of Other Drugs

In a study of 12 healthy volunteers, simvastatin at the 80-mg dose had no effect on the metabolism of the probe cytochrome P450 isoform 3A4 (CYP3A4) substrates midazolam and erythromycin. Simvastatin is not an inhibitor of CYP3A4 and is not expected to affect the plasma levels of other drugs metabolized by CYP3A4.

Coadministration of simvastatin (40 mg QD for 10 days) resulted in an increase in the maximum mean levels of cardioactive digoxin (given as a single 0.4 mg dose on day 10) by approximately 0.3 ng/mL [see Drug Interactions (7.2)].

13 NONCLINICAL TOXICOLOGY

13.1 Carcinogenesis, Mutagenesis, Impairment of Fertility

In a 72-week carcinogenicity study, mice were administered daily doses of simvastatin of 25, 100, and 400 mg/kg body weight, which resulted in mean plasma drug levels approximately 1, 4, and 8 times higher than the mean human plasma drug level, respectively (as total inhibitory activity based on AUC) after an 80-mg oral dose. Liver carcinomas were significantly increased in high-dose females and mid- and high-dose males with a maximum incidence of 90% in males. The incidence of adenomas of the liver was significantly increased in mid- and high-dose females. Drug treatment also significantly increased the incidence of lung adenomas in mid- and high-dose males and females. Adenomas of the Harderian gland (a gland of the eye of rodents) were significantly higher in high-dose mice than in controls. No evidence of a tumorigenic effect was observed at 25 mg/kg/day.

In a separate 92-week carcinogenicity study in mice at doses up to 25 mg/kg/day, no evidence of a tumorigenic effect was observed (mean plasma drug levels were 1 times higher than humans given 80 mg simvastatin as measured by AUC).

In a two-year study in rats at 25 mg/kg/day, there was a statistically significant increase in the incidence of thyroid follicular adenomas in female rats exposed to approximately 11 times higher levels of simvastatin than in humans given 80 mg simvastatin (as measured by AUC).

A second two-year rat carcinogenicity study with doses of 50 and 100 mg/kg/day produced hepatocellular adenomas and carcinomas (in female rats at both doses and in males at 100 mg/kg/day). Thyroid follicular cell adenomas were increased in males and females at both doses; thyroid follicular cell carcinomas were increased in females at 100 mg/kg/day. The increased incidence of thyroid neoplasms appears to be consistent with findings from other statins. These treatment levels represented plasma drug levels (AUC) of approximately 7 and 15 times (males) and 22 and 25 times (females) the mean human plasma drug exposure after an 80 milligram daily dose.

No evidence of mutagenicity was observed in a microbial mutagenicity (Ames) test with or without rat or mouse liver metabolic activation. In addition, no evidence of damage to genetic material was noted in an in vitro alkaline elution assay using rat hepatocytes, a V-79 mammalian cell forward mutation study, an in vitro chromosome aberration study in CHO cells, or an in vivo chromosomal aberration assay in mouse bone marrow.

There was decreased fertility in male rats treated with simvastatin for 34 weeks at 25 mg/kg body weight (4 times the maximum human exposure level, based on AUC, in patients receiving 80 mg/day); however, this effect was not observed during a subsequent fertility study in which simvastatin was administered at this same dose level to male rats for 11 weeks (the entire cycle of spermatogenesis including epididymal maturation). No microscopic changes were observed in the testes of rats from either study. At 180 mg/kg/day, (which produces exposure levels 22 times higher than those in humans taking 80 mg/day based on surface area, mg/m^2), seminiferous tubule degeneration (necrosis and loss of spermatogenic epithelium) was observed. In dogs, there was drug-related testicular atrophy, decreased spermatogenesis, spermatocytic degeneration and giant cell formation at 10 mg/kg/day, (approximately 2 times the human exposure, based on AUC, at 80 mg/day). The clinical significance of these findings is unclear.

14 CLINICAL STUDIES

Adults at High Risk of Coronary Heart Disease Events

In a randomized, double-blind, placebo-controlled, multi-centered study [the Scandinavian Simvastatin Survival Study (Study 4S)], the effect of therapy with ZOCOR on total mortality was assessed in 4,444 adult patients with CHD (history of angina and/or a previous myocardial infarction) and baseline total cholesterol (total-C) between 212 and 309 mg/dL who were on a lipid-lowering diet. In Study 4S, patients were treated with standard care, including lipid-lowering diet, and randomized to either ZOCOR 20-40 mg/day (n=2,221) or placebo (n=2,223) for a median duration of 5.4 years.

- ZOCOR significantly reduced the risk of mortality by 30% (p=0.0003, 182 deaths in the ZOCOR group vs 256 deaths in the placebo group). The risk of CHD mortality was significantly reduced by 42% (p=0.00001, 111 deaths in the ZOCOR group vs 189 deaths in the placebo group). There was no statistically significant difference between groups in non-cardiovascular mortality.
- ZOCOR significantly reduced the risk for the secondary composite endpoint (time to first occurrence of CHD death, definite or probable hospital verified non-fatal MI, silent MI verified by ECG, or resuscitated cardiac arrest) by 34% (p<0.00001, 431 vs 622 patients with one or more events). ZOCOR reduced the risk of major coronary events to a similar extent across the range of baseline total and LDL cholesterol levels. The risk of having a hospital-verified non-fatal MI was reduced by 37%.
- ZOCOR significantly reduced the risk for undergoing myocardial revascularization procedures (coronary artery bypass grafting or percutaneous transluminal coronary angioplasty) by 37% (p<0.00001, 252 vs 383 patients).
- ZOCOR significantly reduced the risk of fatal plus non-fatal cerebrovascular events (combined stroke and transient ischemic attacks) by 28% (p=0.033, 75 vs 102 patients).
- Over the course of the study, treatment with ZOCOR led to mean reductions in total-C, LDL-C and triglycerides (TG) of 25%, 35%, and 10%, respectively, and a mean increase in high-density lipoprotein cholesterol (HDL-C) of 8%. In contrast, treatment with placebo led to increases in total-C, LDL-C and TG of 1%, 1%, and 7%, respectively.
- Because there were only 53 female deaths (approximately 18% of the study population was female), the effect of ZOCOR on mortality in women could not be adequately assessed. However, ZOCOR significantly reduced the risk of having major coronary events in women by 34% (60 vs 91 women with one or more event).
- ZOCOR resulted in similar decreases in relative risk for total mortality, CHD mortality, and major coronary events in geriatric patients (≥65 years) compared with younger adults.

The Heart Protection Study (Study HPS) was a randomized, placebo-controlled, double-blind, multi-centered study with a mean duration of 5 years conducted in 10,269 patients on ZOCOR 40 mg and 10,267 on placebo. Patients had a mean age of 64 years (range 40-80 years old), 97% were white, and were at high risk of developing a major coronary event because of existing CHD (65%), diabetes (Type 2, 26%; Type 1, 3%), history of stroke or other cerebrovascular disease (16%), peripheral vascular disease (33%), or they were males ≥65 years with hypertension in (6%). At baseline:

- 3,421 patients (17%) had LDL-C levels below 100 mg/dL, including 953 (5%) below 80 mg/dL; and
- 10,047 patients (49%) had levels greater than 130 mg/dL.

Patients were randomized to ZOCOR or placebo using a covariate adaptive method which considered the distribution of 10 important baseline characteristics of patients already enrolled.

The Study HPS results showed that ZOCOR 40 mg/day significantly reduced: total and CHD mortality; and non-fatal MI, stroke, and revascularization procedures (coronary and non-coronary) (see Table 5).

Table 5: CHD Mortality and Cardiovascular Events in Adult Patients with High Risk of Developing a Major Coronary Event in Study HPS
Endpoint | ZOCOR (N=10,269) n (%) [n = number of patients with indicated event] | Placebo (N=10,267) n (%) | Risk Reduction (%) (95% CI) | p-Value
Primary
Mortality | 1,328 (12.9%) | 1,507 (14.7%) | 13% (6-19%) | p=0.0003
CHD mortality | 587 (5.7%) | 707 (6.9%) | 18% (8-26%) | p=0.0005
Secondary
Non-fatal MI | 357 (3.5%) | 574 (5.6%) | 38% (30-46%) | p<0.0001
Stroke | 444 (4.3%) | 585 (5.7%) | 25% (15-34%) | p<0.0001
Tertiary
Coronary revascularization | 513 (5%) | 725 (7.1%) | 30% (22-38%) | p<0.0001
Peripheral and other non-coronary revascularization | 450 (4.4%) | 532 (5.2%) | 16% (5-26%) | p=0.006

Two composite endpoints were defined to have enough events to assess relative risk reductions across a range of baseline characteristics:

- Major coronary events (MCE) was comprised of CHD mortality and non-fatal MI. Analyzed by time-to-first event; 898 patients (8.7%) treated with ZOCOR had events and 1,212 patients (11.8%) treated with placebo had events.
- Major vascular events (MVE) was comprised of MCE, stroke, and revascularization procedures including coronary, peripheral and other non-coronary procedures. Analyzed by time-to-first event; 2,033 patients (19.8%) treated with ZOCOR had events and 2,585 patients (25.2%) on placebo had events.

ZOCOR use led to significant relative risk reductions for both composite endpoints (27% for MCE and 24% for MVE, p<0.0001) and for all components of the composite endpoints. The risk reductions produced by ZOCOR in both MCE and MVE were evident and consistent regardless of cardiovascular disease related medical history at study entry (i.e., CHD alone; or peripheral vascular disease, cerebrovascular disease, diabetes or treated hypertension, with or without CHD), gender, age, baseline levels of LDL-C, baseline concomitant cardiovascular medications (i.e., aspirin, beta blockers, or calcium channel blockers), smoking status, or obesity. Patients with diabetes showed risk reductions for MCE and MVE due to ZOCOR treatment regardless of baseline HbA1c levels or obesity.

Primary Hyperlipidemia in Adults

The effects of ZOCOR on total-C and LDL-C were assessed in controlled clinical studies in adult patients with heterozygous familial and non-familial forms of hyperlipidemia and in mixed hyperlipidemia. ZOCOR significantly decreased total-C, LDL-C, and TG, and increased HDL-C (see Table 6). Maximal to near maximal response was generally achieved within 4-6 weeks and maintained during chronic therapy.

Table 6: Mean Changes in Lipid Levels in Adult Patients with Primary Hyperlipidemia and Combined (mixed) Hyperlipidemia (Mean Percent Change from Baseline After 6 to 24 Weeks)
TREATMENT | N | TOTAL-C | LDL-C | HDL-C | TG [median percent change]
Lower Dosage Comparative Study [mean baseline LDL-C = 244 mg/dL and median baseline TG = 168 mg/dL] (Mean % Change at Week 6)
ZOCOR 5 mg once at night | 109 | -19% | -26% | +10% | -12%
ZOCOR 10 mg once at night | 110 | -23% | -30% | +12% | -15%
Scandinavian Simvastatin Survival Study [mean baseline LDL-C = 188 mg/dL and median baseline TG = 128 mg/dL] (Mean % Change at Week 6)
Placebo | 2223 | -1% | -1% | 0% | -2%
ZOCOR 20 mg once at night | 2221 | -28% | -38% | +8% | -19%
Upper Dosage Comparative Study [mean baseline LDL-C = 226 mg/dL and median baseline TG = 156 mg/dL] (Mean % Change Averaged at Weeks 18 and 24)
ZOCOR 40 mg once at night | 433 | -31% | -41% | +9% | -18%
ZOCOR 80 mg once at night [21% and 36% median reduction in TG in patients with TG ≤200 mg/dL and TG >200 mg/dL, respectively. Patients with TG >350 mg/dL were excluded] | 664 | -36% | -47% | +8% | -24%
Combined Hyperlipidemia Study [mean baseline LDL-C = 156 mg/dL and median baseline TG = 391 mg/dL.] (Mean % Change at Week 6)
Placebo | 125 | 1% | 2% | +3% | -4%
ZOCOR 40 mg once at night | 123 | -25% | -29% | +13% | -28%
ZOCOR 80 mg once at night | 124 | -31% | -36% | +16% | -33%

Hypertriglyceridemia in Adults

The results of a subgroup analysis in 74 adult patients with hypertriglyceridemia from a 130-patient, double-blind, placebo-controlled, 3-period crossover study are similar to those presented in Table 6 for the Combined Hyperlipidemia Study. ZOCOR decreased TC, LDL-C, and TG in these patients.

Dysbetalipoproteinemia in Adults

The results of a subgroup analysis in 7 adult patients with dysbetalipoproteinemia (apo E2/2) (very-low-density lipoprotein cholesterol [VLDL-C]/TG>0.25) from a 130-patient, double-blind, placebo-controlled, 3-period crossover study are presented in Table 7. ZOCOR decreased total-C, LDL-C + intermediate-density lipoprotein (IDL), VLDL-C + IDL, and TG compared to placebo.

Table 7: Lipid Effects in Adult Patients with Dysbetalipoproteinemia Over Six Weeks [Median Percent Change (min, max) from Baseline] [The median baseline values (mg/dL) were: total-C = 324, LDL-C = 121, HDL-C = 31, TG = 411, VLDL-C = 170, and non-HDL-C = 291.]
TREATMENT | N | Total-C | LDL-C + IDL | HDL-C | TG | VLDL-C + IDL | Non-HDL-C
Placebo | 7 | -8% (-24, +34) | -8% (-27, +23) | -2% (-21, +16) | +4% (-22, +90) | -4% (-28, +78) | -8% (-26, -39)
ZOCOR 40 mg/day | 7 | -50% (-66, -39) | -50% (-60, -31) | +7% (-8, +23) | -41% (-74, -16) | -58% (-90, -37) | -57% (-72, -44)
ZOCOR 80 mg/day | 7 | -52% (-55, -41) | -51% (-57, -28) | +7% (-5, +29) | -38% (-58, +2) | -60% (-72, -39) | -59% (-61, -46)

Homozygous Familial Hypercholesterolemia

In a controlled clinical study, 12 patients 15-39 years of age with homozygous familial hypercholesterolemia (HoFH) received ZOCOR 40 mg/day in a single dose, or 80 mg/day in 3 divided doses. In 12 patients the mean LDL-C changes at 9 weeks for the 40- and 80-mg doses were -13.7% (range -22.5% to -4.9%) and -24.6% (range -37.3% to -11.9%), respectively.

Pediatric Patients 10 Years of Age and Older with HeFH

In a double-blind, placebo-controlled study, 175 pediatric patients (99 boys and 76 post-menarchal girls) 10 years of age and older (mean age 14 years old) with heterozygous familial hypercholesterolemia (HeFH) were randomized to ZOCOR (n=106) or placebo (n=67) for 24 weeks (base study). To be included in the study, patients were required to have a baseline LDL-C level between 160 and 400 mg/dL and at least one parent with an LDL-C level >189 mg/dL. The dosage of ZOCOR (once daily in the evening) was 10 mg for the first 8 weeks, 20 mg for the second 8 weeks, and 40 mg thereafter. In a 24-week extension, 144 patients elected to continue therapy with ZOCOR 40 mg or placebo.

ZOCOR significantly decreased plasma levels of total-C, LDL-C, and apolipoprotein B (ApoB) (see Table 8) in the HeFH study. Results from the extension at 48 weeks were comparable to the results at Week 24.

The safety and effectiveness of dosages above 40 mg daily have not been studied in pediatric patients with HeFH. The long-term efficacy of ZOCOR therapy in pediatric patients to reduce morbidity and mortality in adulthood has not been established.

Table 8: Lipid Effects in Pediatric Patients 10 Years of Age and Older with Heterozygous Familial Hypercholesterolemia (Mean Percent Change from Baseline)
Dosage | Duration | N |  | Total-C | LDL-C | HDL-C | TG [median percent change] | ApoB
Placebo | 24 Weeks | 67 | % Change from Baseline (95% CI) | +1.6% (-2.2, 5.3) | +1.1% (-3.4, 5.5) | +3.6% (-0.7, 8.0) | -3.2% (-11.8, 5.4) | -0.5% (-4.7, 3.6)
Placebo | 24 Weeks | 67 | Mean baseline, mg/dL (SD) | 279 (52) | 212 (49) | 47 (12) | 90 (51) | 186 (38)
ZOCOR | 24 Weeks | 106 | % Change from Baseline (95% CI) | -26.5% (-29.6, -23.3) | -36.8% (-40.5, -33.0) | +8.3% (4.6, 11.9) | -7.9% (-15.8, 0.0) | -32.4% (-35.9, -29.0)
ZOCOR | 24 Weeks | 106 | Mean baseline, mg/dL (SD) | 270 (44) | 204 (42) | 48 (9) | 78 (46) | 180 (34)

16 HOW SUPPLIED/STORAGE AND HANDLING

ZOCOR tablets are supplied as follows:

Strength [The 5 mg and 80 mg strengths of ZOCOR are no longer marketed.] | How Supplied | NDC | Tablet Description
10 mg | unit of use bottles of 30 | 78206-180-01 | peach, oval, marked MSD 735 on one side and plain on the other
10 mg | unit of use bottles of 90 | 78206-180-02 | peach, oval, marked MSD 735 on one side and plain on the other
20 mg | unit of use bottles of 30 | 78206-181-01 | tan, oval, marked MSD 740 on one side and plain on the other
20 mg | unit of use bottles of 90 | 78206-181-02 | tan, oval, marked MSD 740 on one side and plain on the other
40 mg | unit of use bottles of 30 | 78206-182-01 | brick red, oval, marked MSD 749 on one side and plain on the other
40 mg | unit of use bottles of 90 | 78206-182-02 | brick red, oval, marked MSD 749 on one side and plain on the other

Storage

Store between 41°F to 86°F (5°C to 30°C).

17 PATIENT COUNSELING INFORMATION

Advise the patient to read the FDA-approved patient labeling (Patient Information).

Myopathy and Rhabdomyolysis
Advise patients that ZOCOR may cause myopathy and rhabdomyolysis. Inform patients taking an 80 mg daily dose of ZOCOR that they are at an increased risk. Inform patients that the risk is also increased when taking certain types of medication or consuming grapefruit juice and they should discuss all medication, both prescription and over the counter, with their healthcare provider. Instruct patients to inform other healthcare providers prescribing a new medication or increasing the dose of an existing medication that they are taking ZOCOR. Instruct patients to promptly report any unexplained muscle pain, tenderness or weakness particularly if accompanied by malaise or fever [see Contraindications (4), Warnings and Precautions (5.1), and Drug Interactions (7.1)].

Hepatic Dysfunction
Inform patients that ZOCOR may cause liver enzyme elevations and possibly liver failure. Advise patients to promptly report fatigue, anorexia, right upper abdominal discomfort, dark urine or jaundice [see Warnings and Precautions (5.3)].

Increases in HbA1c and Fasting Serum Glucose Levels
Inform patients that increases in HbA1c and fasting serum glucose levels may occur with ZOCOR. Encourage patients to optimize lifestyle measures, including regular exercise, maintaining a healthy body weight, and making healthy food choices [see Warnings and Precautions (5.4)].

Pregnancy
Advise pregnant patients and patients who can become pregnant of the potential risk to a fetus. Advise patients to inform their healthcare provider of a known or suspected pregnancy to discuss if ZOCOR should be discontinued [see Use in Specific Populations (8.1)].

Lactation
Advise patients that breastfeeding is not recommended during treatment with ZOCOR [see Use in Specific Populations (8.2)].

Missed Dose
Instruct patients to take ZOCOR only as prescribed. If a dose is missed, it should be taken as soon as possible. Advise patients not to double their next dose.

Manufactured for: Organon LLC, a subsidiary of
ORGANON & Co.,
Jersey City, NJ 07302, USA

For patent information: www.organon.com/our-solutions/patent/

© 2023 Organon group of companies. All rights reserved.

uspi-og0733-t-2308r004

PATIENT INFORMATION
ZOCOR® (zOH-kor)
(simvastatin)
tablets, for oral use

Read this Patient Information before you start taking ZOCOR and each time you get a refill. There may be new information. This information does not take the place of talking with your healthcare provider about your medical condition or your treatment.

What is ZOCOR?

ZOCOR is a prescription medicine that contains the cholesterol lowering medicine, simvastatin.

ZOCOR is used to lower:

- the risk of death by lowering the risk of heart disease death.
- the risk of heart attacks and strokes.
- the need for certain types of heart and blood vessel procedures to improve blood flow called arterial revascularization in people with known heart, cerebrovascular disease (conditions that affect blood flow and the blood vessels in the brain), peripheral vascular disease (a blood circulation disorder that causes the blood vessels outside of your heart and brain to narrow, block, or spasm), and diabetes, who are at high risk for heart disease problems.

ZOCOR is used along with diet to:

- lower the level of low-density lipoprotein (LDL) cholesterol or “bad” cholesterol in adults with hyperlipidemia (high levels of fat in the blood), and in adults and children 10 years of age and older with heterozygous familial hypercholesterolemia (an inherited condition that causes high levels of LDL).
- treat adults with a type of high cholesterol called primary dysbetalipoproteinemia.
- lower the level of triglycerides (type of fat in the blood) in adults.

ZOCOR is used along with other cholesterol lowering treatments to lower the level of low-density lipoprotein (LDL) in adults with a type of high cholesterol called homozygous familial hypercholesterolemia (an inherited condition that causes high levels of LDL).

The safety and effectiveness of ZOCOR has not been established in children younger than 10 years of age with heterozygous familial hypercholesterolemia (HeFH) or other types of hyperlipidemia (high levels of fat in the blood).

Do not take ZOCOR if you:

- take certain medicines called CYP3A4 inhibitors such as:
  - certain antifungal medicines (such as itraconazole, ketoconazole, posaconazole, voriconazole).
  - certain antibiotics (including erythromycin, clarithromycin).
  - HIV protease inhibitors (such as indinavir, nelfinavir, ritonavir, and darunavir/ritonavir) and cobicistat-containing products such as (elvitegravir/cobicistat/emtricitabine/tenofovir disoproxil fumarate).
  - certain hepatitis C virus protease inhibitors (such as boceprevir or telaprevir).
  - the antidepressant nefazodone.
- take medicines called cyclosporine, danazol, or gemfibrozil.
- have liver problems.
- are allergic to simvastatin or any of the ingredients in ZOCOR. See the end of this Patient Information leaflet for a complete list of ingredients in ZOCOR.

Ask your healthcare provider or pharmacist if you are not sure if your medicine is listed above.

Before you take ZOCOR, tell your healthcare provider about all of your medical conditions, including if you:

- have unexplained muscle aches or weakness.
- have or have had myasthenia gravis (a disease causing general muscle weakness including in some cases muscles used for breathing), ocular myasthenia (a disease causing eye muscle weakness).
- have kidney problems.
- have liver problems or drink more than 2 glasses of alcohol daily.
- have thyroid problems.
- are 65 years of age or older.
- are of Chinese descent.
- are pregnant or plan to become pregnant. If you become pregnant while taking ZOCOR, call your healthcare provider right away to discuss stopping ZOCOR.
- are breastfeeding or plan to breastfeed. It is not known if ZOCOR passes into your breast milk. Do not breastfeed while taking ZOCOR.

Tell your healthcare provider about all the medicines you take, including prescription and over-the-counter medicines, vitamins, and herbal supplements. Talk to your healthcare provider before you start taking any new medicines.

Tell your healthcare provider who prescribes ZOCOR if another healthcare provider increases the dose of another medicine you are taking.

ZOCOR may affect the way other medicines work, and other medicines may affect how ZOCOR works. Especially tell your healthcare provider if you take:

- digoxin (a drug used to treat irregular heartbeat).
- coumarin anticoagulants (drugs that prevent blood clots, such as warfarin).

Taking ZOCOR with certain substances can also increase the risk of muscle problems. Especially tell your healthcare provider if you take:

- amiodarone or dronedarone (medicines used to treat an irregular heartbeat).
- verapamil, diltiazem, amlodipine, or ranolazine (medicines used to treat high blood pressure, chest pain associated with heart disease, or other heart conditions).
- lomitapide (a medicine used to treat a serious and rare genetic cholesterol condition).
- daptomycin (a drug used to treat complicated skin and bloodstream infections).
- large doses of niacin or nicotinic acid, especially if you are of Chinese descent.
- fibric acid derivatives (such as fenofibrate).
- colchicine (a medicine used to treat gout).
- grapefruit juice.

Ask your healthcare provider or pharmacist for a list of medicines if you are not sure. Know the medicines you take. Keep a list of them to show your healthcare provider and pharmacist when you get a new medicine.

How should I take ZOCOR?

- Take ZOCOR exactly as your healthcare provider tells you to take it.
- Do not change your dose or stop taking ZOCOR without talking to your healthcare provider.
- Take ZOCOR 1 time each day in the evening.
- If you miss a dose, take it as soon as you remember. If you do not remember until it is time for your next dose, skip the missed dose and go back to your regular schedule. Do not take 2 doses of ZOCOR at the same time. Talk with your healthcare provider if you have questions about a missed dose.
- While taking ZOCOR, continue to follow your cholesterol-lowering diet and to exercise as your healthcare provider told you to.
- Your healthcare provider may do blood tests to check your cholesterol while you take ZOCOR. Your healthcare provider may change your dose of ZOCOR if needed.
- In case of overdose, get medical help or contact a live Poison Center expert right away at 1-800-222-1222. Advice is also available online at poisonhelp.org

What are the possible side effects of ZOCOR?

ZOCOR may cause serious side effects including:

- Muscle pain, tenderness, and weakness (myopathy). Muscle problems, including muscle breakdown, can be serious in some people and rarely cause kidney damage that can lead to death.
  Tell your healthcare provider right away if:
  - you have unexplained muscle pain, tenderness, or weakness, especially if you have a fever or feel more tired than usual, while you take ZOCOR.
  - you have muscle problems that do not go away even after your healthcare provider has advised you to stop taking ZOCOR. Your healthcare provider may do further tests to diagnose the cause of your muscle problems.
    Your chances of getting muscle problems are higher if you:
  - are taking certain other medicines while you take ZOCOR.
  - are 65 years of age or older.
  - are female.
  - have thyroid problems (hypothyroidism) that are not controlled.
  - have kidney problems.
  - are taking higher doses of ZOCOR.
  - are Chinese.
- Liver problems. Your healthcare provider should do blood tests to check your liver before you start taking ZOCOR and if you have any symptoms of liver problems while you take ZOCOR. Call your healthcare provider right away if you have the following symptoms of liver problems:
  - feeling tired or weak
  - loss of appetite
  - right-sided upper belly pain
  - dark urine
  - yellowing of your skin or the whites of your eyes
- Increase in blood sugar (glucose) levels). ZOCOR may cause an increase in your blood sugar levels.

The most common side effects of ZOCOR include:

- upper respiratory infection
- headache
- stomach (abdominal) pain
- constipation
- nausea

Tell your healthcare provider if you have any side effect that bothers you or does not go away.

These are not all the possible side effects of ZOCOR.

Call your doctor for medical advice about side effects. You may report side effects to FDA at 1-800-FDA-1088.

How should I store ZOCOR?

- Store ZOCOR between 41°F to 86°F (5°C to 30°C).

Keep ZOCOR and all medicines out of the reach of children.

General information about safe and effective use of ZOCOR.

Medicines are sometimes prescribed for purposes other than those listed in a Patient Information leaflet. Do not use ZOCOR for a condition for which it was not prescribed. Do not give ZOCOR to other people, even if they have the same symptoms that you have. It may harm them.

You can ask your pharmacist or healthcare provider for information about ZOCOR that is written for health professionals.

What are the ingredients in ZOCOR?

Active ingredient: simvastatin.

Inactive ingredients: ascorbic acid, citric acid, hydroxypropyl cellulose, hypromellose, iron oxides, lactose, magnesium stearate, microcrystalline cellulose, starch, talc, and titanium dioxide. Butylated hydroxyanisole is added as a preservative.

Manufactured for: Organon LLC, a subsidiary of
ORGANON & Co.,
Jersey City, NJ 07302, USA

For patent information: www.organon.com/our-solutions/patent/

© 2023 Organon group of companies. All rights reserved.

For more information, go to www.organon.com/our-focus/products-list/ or call 1-844-674-3200.

usppi-og0733-t-2308r001

This Patient Information has been approved by the U.S. Food and Drug Administration.

Revised: 8/2023

PRINCIPAL DISPLAY PANEL - 10 mg Tablet Bottle Label

NDC 78206-180-01

Zocor®
(Simvastatin) Tablets

10 mg

Each tablet contains 10 mg of simvastatin.

Rx only

30 Tablets

PRINCIPAL DISPLAY PANEL - 20 mg Tablet Bottle Label

NDC 78206-181-01

Zocor®
(Simvastatin) Tablets

20 mg

Each tablet contains 20 mg of simvastatin.

Rx only

30 Tablets

PRINCIPAL DISPLAY PANEL - 40 mg Tablet Bottle Label

NDC 78206-182-01

Zocor®
(Simvastatin) Tablets

40 mg

Each tablet contains 40 mg of simvastatin.

Rx only

30 Tablets